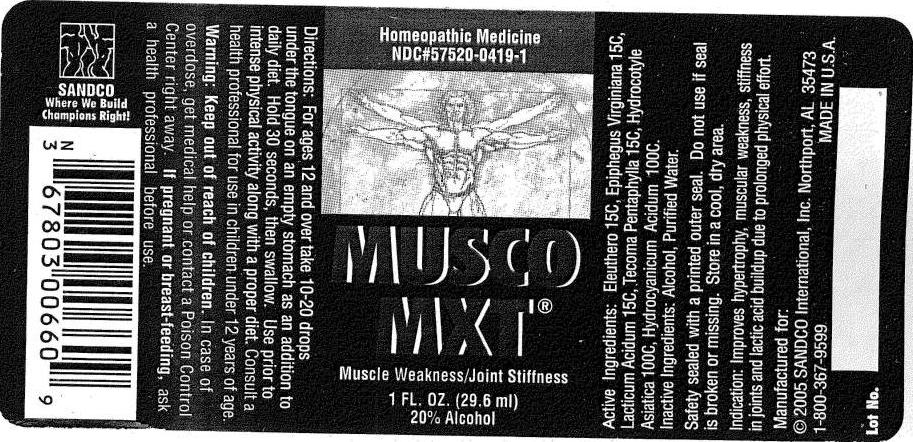 DRUG LABEL: Musco
NDC: 57520-0419 | Form: LIQUID
Manufacturer: Apotheca Company
Category: homeopathic | Type: HUMAN OTC DRUG LABEL
Date: 20110628

ACTIVE INGREDIENTS: ELEUTHERO 15 [hp_C]/1 mL; LACTIC ACID, DL- 15 [hp_C]/1 mL; CENTELLA ASIATICA 100 [hp_C]/1 mL; HYDROGEN CYANIDE 100 [hp_C]/1 mL; EPIFAGUS VIRGINIANA     15 [hp_C]/1 mL; TABEBUIA HETEROPHYLLA BARK     15 [hp_C]/1 mL
INACTIVE INGREDIENTS: WATER; ALCOHOL

Musco MXT

ACTIVE INGREDIENT

ACTIVE INGREDIENTS: Eleuthero 15C, Epiphegus virginiana 15C, Lacticum acidum 15C, Tecoma pentaphylla 15C, Hydrocotyle asiatica 100C, Hydrocyanicum acidum 100C.

PURPOSE

INDICATIONS: Improves hypertrophy, muscular weakness, stiffness in joints and lactic acid buildup due to prolonged physical effort.

WARNINGS

WARNINGS: Keep out of reach of children. In case of overdose, get medical help or contact a Poison Control Center right away.

If pregnant or breast-feeding, ask a health professional before use.

Safety sealed with a printed outer seal. Do not use if seal is broken or missing. Store in a cool, dry place.

DOSAGE AND ADMINISTRATION

DIRECTIONS: For ages 12 and over take 10-20 drops under the tongue on an empty stomach as an addition to daily diet. Hold 30 seconds, then swallow. Use prior to intense physical activity along with a proper diet. Consult a health professional for use in children under 12 years of age.

INACTIVE INGREDIENTS: Alcohol, Purified water

KEEP OUT OF REACH OF CHILDREN. In case of overdose, get medical help or contact a Poison Control Center right away.

INDICATIONS AND USAGE

INDICATIONS: Improves hypertrophy, muscular weakness, stiffness in joints and lactic acid buildup due to prolonged physical effort.

QUESTIONS

Manufactured for:

SANDCO International, Inc.

Northport, AL 35473

1-800-367-9599

PACKAGE LABEL

Homeopathic Medicine

NDC#57520-0419-1

MUSCO MXT

Muscle Weakness/Joint Stiffness

1 FL. OZ.(29.6 ml)